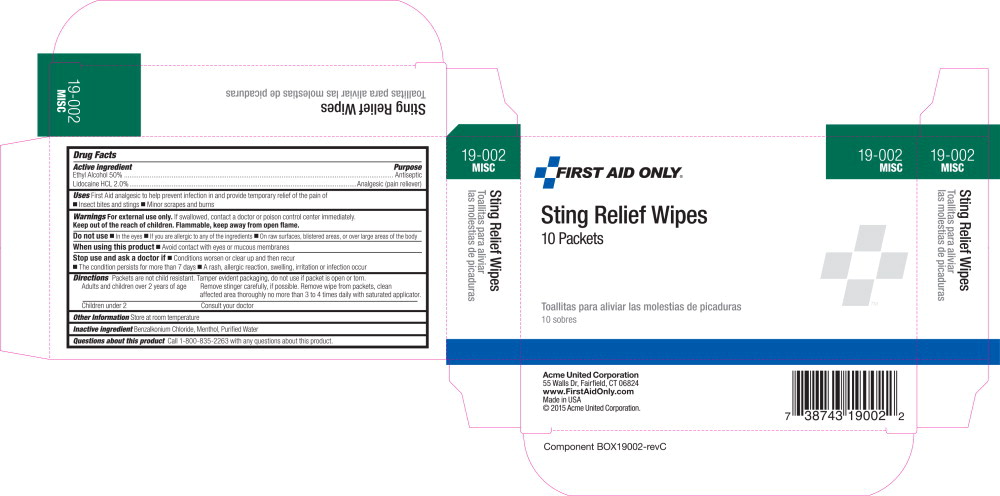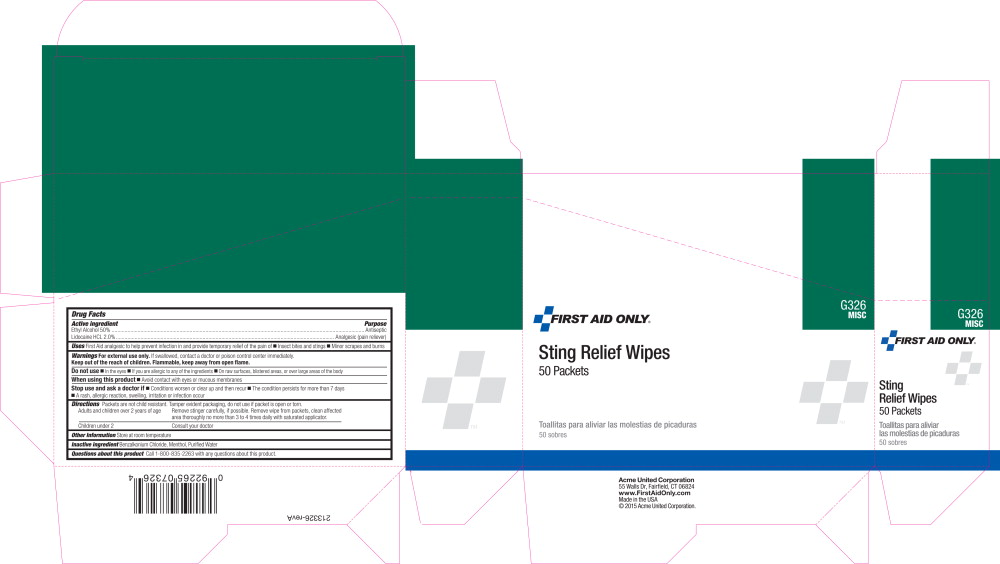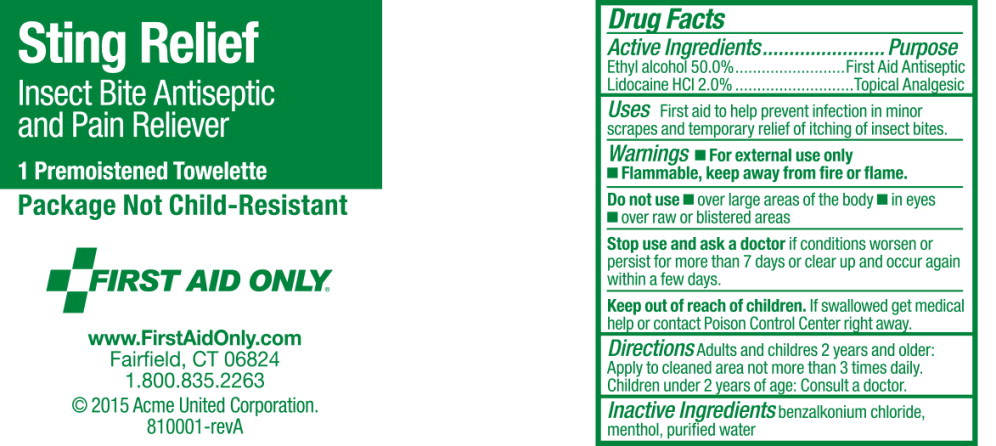 DRUG LABEL: Sting Relief
NDC: 0924-5200 | Form: CLOTH
Manufacturer: Acme United Corporation
Category: otc | Type: HUMAN OTC DRUG LABEL
Date: 20160222

ACTIVE INGREDIENTS: alcohol 0.50 mL/1 mL; lidocaine hydrochloride 20 mg/1 mL
INACTIVE INGREDIENTS: benzalkonium chloride; menthol; water

Drug Facts

Active Ingredient:

Ethyl Alcohol 50.0%

Lidocaine HCl 2.0%

Purpose:

Antiseptic

Analgesic (pain reliever)

Uses

First aid analgesic to help prevent infection in and provide temporary relief of the pain of:

- Insect bites and stings
- Minor scrapes and burns

Warnings:

For external use only. If swallowed, contact a doctor or poison control center immediately.

KEEP OUT OF REACH OF CHILDREN

Keep out of the reach of children. Flammable, keep away from open flame.

DO NOT USE:

- In the eyes
- If you are allergic to any of the ingredients
- On raw surfaces, blistered areas, or over large areas of the body

WHEN USING THIS PRODUCT:

- Avoid contact with eyes or mucous membranes

STOP USE AND ASK A DOCTOR IF:

- Conditions worsen clear up and then recur
- The condition persists for more than 7 days
- A rash, allergic reaction, swelling, irritation or infection occur

Directions:

Packets are not child resistant. Tamper evident packaging, do not use if packet is opened or torn.

Adults and children: over 2 years of age:

Remove stinger carefully, if possible. Remove wipe from packet, clean affected area thoroughly no more than 3 times daily with saturated applicator.

Children under 2:

Consult your doctor.

Other information:

Store at room temperature.

Inactive ingredients:

Benzalkonium Chloride, Menthol, Purified Water

Questions about this product:

Call 800-835-2263 with any questions about this product.

Principal Display Panel - Carton Label

19-002

MISC

FIRST AID ONLY®

Sting Relief Wipes

10 Packets

Toallitas para aliviar las molestias de picaduras

10 sobres

Principal Display Panel - Carton Label

G326

MISC

FIRST AID ONLY®

Sting Relief Wipes

50 Packets

Toallitas para aliviar las molestias de picaduras

50 sobres

Principal Display Panel - Packet Label

Sting Relief

Insect Bite Antiseptic
and Pain Reliever

1 Premoistened Towlette

Package Not Child-Resistant

FIRST AID ONLY®

www.FirstAidOnly.com

Fairfield, CT 06824

1.800.835.2263

© Acme United Corporation.

810001-revA